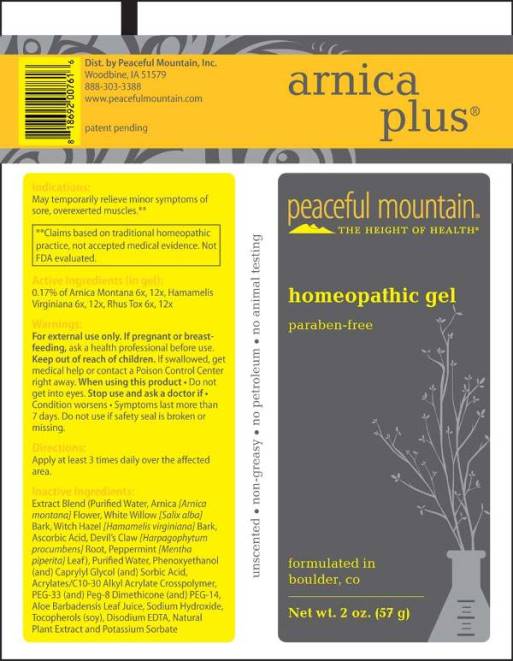 DRUG LABEL: Arnica Plus
NDC: 43846-0075 | Form: GEL
Manufacturer: Peaceful Mountain, Inc.
Category: homeopathic | Type: HUMAN OTC DRUG LABEL
Date: 20230807

ACTIVE INGREDIENTS: ARNICA MONTANA WHOLE 6 [hp_X]/1 g; HAMAMELIS VIRGINIANA ROOT BARK/STEM BARK 6 [hp_X]/1 g; TOXICODENDRON PUBESCENS LEAF 6 [hp_X]/1 g
INACTIVE INGREDIENTS: WATER; PHENOXYETHANOL; CAPRYLYL GLYCOL; SORBIC ACID; SODIUM HYDROXIDE; POLYETHYLENE GLYCOL 1600; PEG-8 DIMETHICONE; POLYETHYLENE GLYCOL 700; ALOE VERA LEAF; .ALPHA.-TOCOPHEROL; EDETATE DISODIUM; OREGANO; POTASSIUM SORBATE; ARNICA MONTANA FLOWER; SALIX ALBA BARK; HAMAMELIS VIRGINIANA BARK; ASCORBIC ACID; HARPAGOPHYTUM PROCUMBENS ROOT; MENTHA PIPERITA LEAF; CARBOMER INTERPOLYMER TYPE A (ALLYL SUCROSE CROSSLINKED); ALCOHOL; SODIUM BENZOATE; CITRIC ACID MONOHYDRATE

DRUG FACTS:

ACTIVE INGREDIENTS:

0.17% of Arnica Montana 6X, 12X, Hamamelis Virginiana 6X, 12X, Rhus Tox 6X, 12X

INDICATIONS:

May temporarily relieve minor symptoms of sore, overexerted muscles.**

**Claims based on traditional homeopathic practice, not accepted medical evidence. Not FDA evaluated.

WARNINGS:

For external use only.

If pregnant or breast-feeding, ask a health professional before use.

Keep out of reach of children. If swallowed, get medical help or contact a Poison Control Center right away.

When using this product • Do not get into eyes.

Stop use and ask a doctor if • Conditions worsens • Symptoms last more than 7 days.

Do not use if safety seal is broken or missing.

Keep out of reach of children. If swallowed, get medical help or contact a Poison Control Center right away.

DIRECTIONS:

Apply at least 3 times daily over the affected area.

INDICATIONS:

May temporarily relieve minor symptoms of sore, overexerted muscles.**

**Claims based on traditional homeopathic practice, not accepted medical evidence. Not FDA evaluated.

INACTIVE INGREDIENTS:

Water, Arnica (Arnica Montana) Flower, White Willow (Salix Alba) Bark, Witch Hazel (Hamamelis Virginiana) Bark, Ascorbic Acid, Devil’s Claw (Harpagophytum Procumbens) Root, Peppermint (Mentha Piperita) Leaf, Acrylates/C10-30 Alkyl acrylate Crosspolymer, Alkyl Acrylate Crosspolymer, Aloe Vera Leaf Juice, Phenoxyethanol, Caprylyl Glycol, Sorbic Acid, Peg-33, Peg-8 Dimethicone, Peg-14, Sodium Hydroxide, Tocopherols (soy), Disodium EDTA, Natural Plant Extract, Potassium Sorbate, Sodium Benzoate, Ethanol, Citric Acid.

QUESTIONS:

Dist. by Peaceful Mountain, Inc.
Woodbine, IA 51579

888-303-3388
www.peacefulmountain.com

PACKAGE LABEL DISPLAY:

arnica plus

peaceful mountain

THE HEIGHT OF HEALTH

homeopathic gel

paraben-free

Net wt. 2 oz. (57 g)